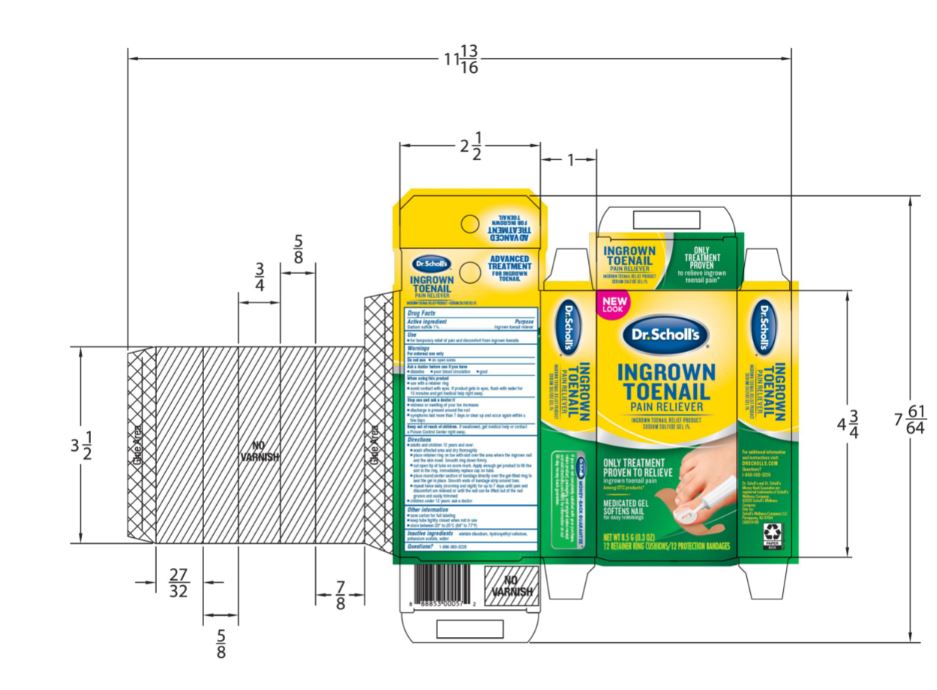 DRUG LABEL: Scholls Wellness Company LLC
NDC: 73469-0062 | Form: GEL
Manufacturer: Scholls Wellness Company LLC
Category: otc | Type: HUMAN OTC DRUG LABEL
Date: 20231009

ACTIVE INGREDIENTS: SODIUM SULFIDE 1 g/100 g
INACTIVE INGREDIENTS: POTASSIUM ACETATE; WATER; EDETATE DISODIUM; HYDROXYETHYL CELLULOSE, UNSPECIFIED

90000062 Ingrown Toenail

Active Ingredient Purpose

Sodium sulfide 1%........................Ingrown toenail reliever

Purpose

Ingrown toenail reliever

Use

for temporary relief of pain and discomfort from ingrown toenails

Warnings

For external use only

Do not use

- on open sores

Ask a doctor before use if you have

- diabetes
- poor blood circulation
- gout

When using this product

- use with a retainer ring
- avoid contact with eyes. If product gets in eyes, flush with water for 15 minutes and get medical help right away.

Stop use and ask a doctor if

- redness or swelling of your toe increases
- discharge is present around the nail
- symptoms last more than 7 days or clear up and occur again within a few days

Keep out of reach of children. If swallowed, get medical help or contact a Poisen Control Center right away.

Directions

adults and children 12 years and over:

wash affected area and dry thoroughly

place retainer ring on toe with slot over the area where the ingrown nail and the skin meet. Smooth ring down firmly.

cut open tip of tube on score mark. Apply enough gel product to fill the slot in the ring. Immediately replace cap on tube.

place round center section of bandage directly over the gel-filled ring to seal the gel in place. Smooth ends of bandage strip around toe.

repeat twice daily (morning and night) for up to 7 days until pain and discomfort is relieved or until the nail can be lifted out of the nail groove and easily trimmed.

children under 12 years: ask a doctor

Other information

- save carton for full labeling
- keep tube tightly closed when not in use
- store between 20º to 25ºC (68º to 77ºF)

Inactive ingredients

edetate disodium, hydroxyethyl cellulose, potassium acetate, water

Questions

Questions? 1-866-360-3226